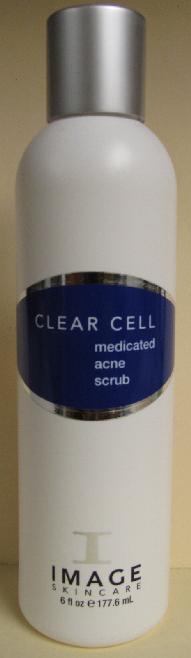 DRUG LABEL: CLEAR CELL Medicated Acne Scrub
NDC: 62742-4034 | Form: CREAM
Manufacturer: Allure Labs, Inc.
Category: otc | Type: HUMAN OTC DRUG LABEL
Date: 20100701

ACTIVE INGREDIENTS: BENZOYL PEROXIDE 30 mg/1 mL

Drug Facts

Active Ingredient:

Benzoyl Peroxide 3%

Inactive Ingredients:

Water, Cocamidopropyl Hydroxysultane, Micro-Exfoliant Beads, Cera Alba (Bees Wax), Ammonium Laureth Sulfate, Glycerin, Aloe Barbadensis (Aloe Vera) Leaf Extract, Melia Azadirachta (Neem) Leaf Extract, Symphytum Officinale (Comfrey) Extract, Carbomer, Triethanolamine, Mentha Virdis (Spearmint) Oil, Melaleuca Alternifolia (Tea Tree) Leaf Oil, Eucalyptus Globulus (Eucalyptus) Leaf Oil, Camellia Sinensis (Green Tea) Leaf Extract, Arnica Montana (Arnica) Flower Extract, Chamomilla Recutita (Chamomile) Flower Extract, Aesculus Hippocastanum (Horse Chestnut) Extract, Allantoin, Disodium EDTA.

Other Information on the back of the container:
(Claims)

A micro-exfoliating cleanser with benoyl peroxide to treat active acne. A blend of anti-oxidants soothe irritated and red, inflamed lesions leaving skin healthy and blemish free.
Paraben-free
Directions:
Apply a liberal amount to wet face and massage for 1 minute. This gentle exfoliation process assists in reducing active acne and thoroughly cleansing oily skin. Rinse with cold water. Use morning and evening. Note: Do not overstimulate active lesions.
Indications:
Active acne and acne-prone skin.

Distributor:
Image International

Palm Beach, FL 33411 USA

www.imageskincare.com

Image of the Product:

CLEAR CELL Medicated Acne Scrub: